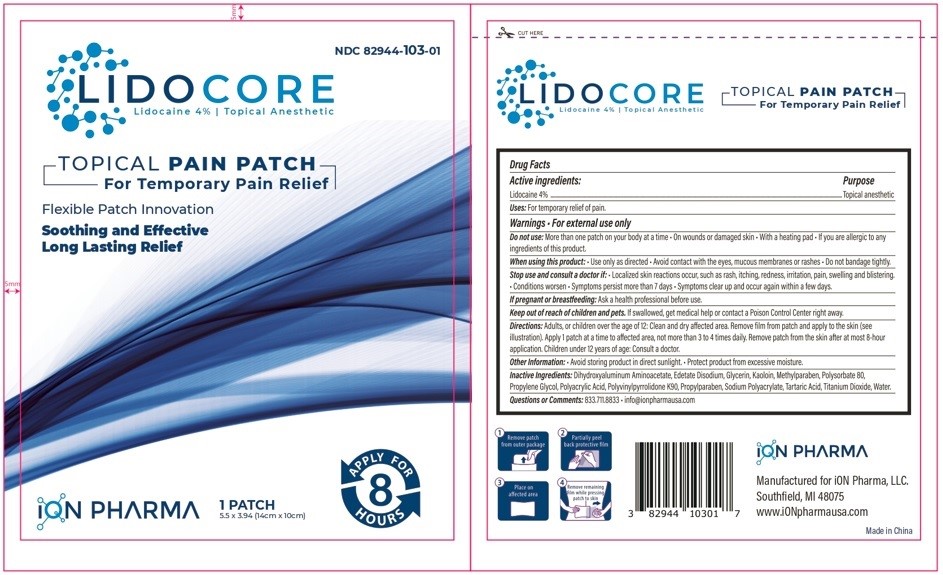 DRUG LABEL: LIDOCORE (single unit patch)
NDC: 82944-103 | Form: PATCH
Manufacturer: Ion Pharma, LLC
Category: otc | Type: HUMAN OTC DRUG LABEL
Date: 20260114

ACTIVE INGREDIENTS: LIDOCAINE 4 g/1 1
INACTIVE INGREDIENTS: DIHYDROXYALUMINUM AMINOACETATE; EDETATE DISODIUM; GLYCERIN; KAOLIN; METHYLPARABEN; POLYSORBATE 80; PROPYLENE GLYCOL; POLYACRYLIC ACID (450000 MW); POVIDONE K90; PROPYLPARABEN; SODIUM POLYACRYLATE (2500000 MW); TARTARIC ACID; TITANIUM DIOXIDE; WATER

LIDOCORE (SINGLE UNIT PATCH)
Lidocaine 4% Topical Anesthetic
TOPICAL PAIN PATCH
For Temporary Pain Relief

Active ingredients:

Lidocaine 4%

Purpose

Topical anesthetic

INDICATIONS AND USAGE

Uses:For temporary relief of pain.

Warnings

- For external use only

Do not use:

- More than one patch on your body at a time
- On wounds or damaged skin
- With a heating pad
- If you are allergic to any ingredients of this product.

When using this product:

- Use only as directed
- Avoid contact with the eyes, mucous membranes or rashes
- Do not bandage tightly.

Stop use and consult a doctor if:

- Localized skin reactions occur, such as rash, itching, redness, irritation, pain, swelling and blistering.
- Conditions worsen
- Symptoms persist more than 7 days
- Symptoms clear up and occur again within a few days.

PREGNANCY OR BREAST FEEDING

If pregnant or breastfeeding:Ask a health professional before use.

Keep out of reach of children and pets.If swallowed, get medical help or contact a Poison Control Center right away.

DOSAGE AND ADMINISTRATION

Directions:Adults, or children over the age of 12: Clean and dry affected area. Remove film from patch and apply to the skin (see illustration). Apply 1 patch at a time to affected area, not more than 3 to 4 times daily. Remove patch from the skin after at most 8-hour application. Children under 12 years of age: Consult a doctor.

Other Information:

- Avoid storing product in direct sunlight.
- Protect product from excessive moisture.

INACTIVE INGREDIENT

Inactive Ingredients:Dihydroxyaluminum Aminoacetate, Edetate Disodium, Glycerin, Kaoloin, Methylparaben, Polysorbate 80, Propylene Glycol, Polyacrylic Acid, Polyvinylpyrrolidone K90, Propylparaben, Sodium Polyacrylate, Tartaric Acid, Titanium Dioxide, Water.

Questions or comments:833.711.8833

- info@ionpharmausa.com

PRINCIPAL DISPLAY PANEL

NDC 82944-103-01

LIDOCORE
Lidocaine 4% Topical Anesthetic

TOPICAL PAIN PATCH
For Temporary Pain Relief

Flexible Patch Innovation

Soothing and Effective
Long Lasting Relief

1 PATCH
5.5 x 3.94 (14cm x 10cm)

APPLY FOR 8 HOURS

ION PHARMA